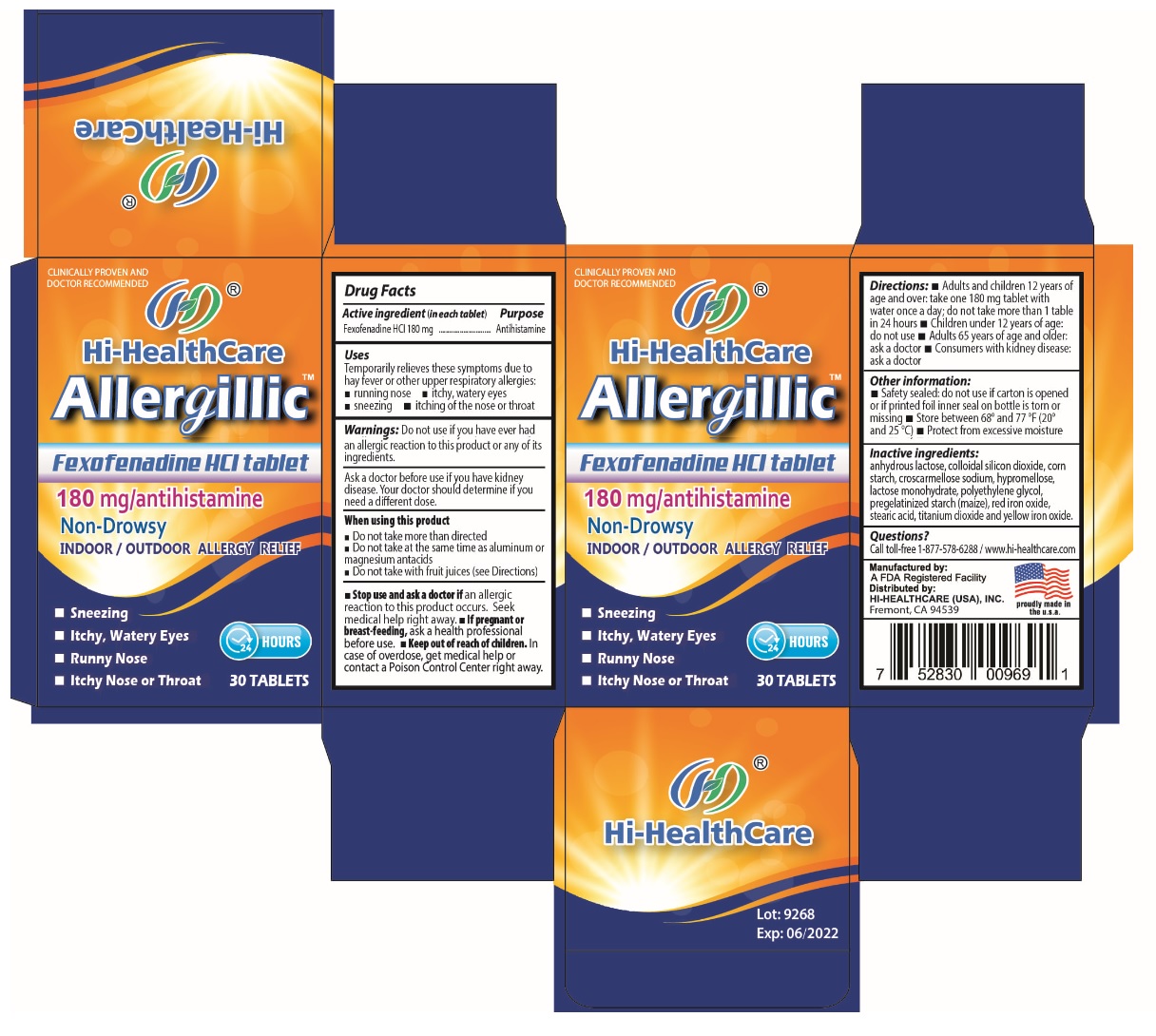 DRUG LABEL: Allergillic
NDC: 77684-628 | Form: TABLET
Manufacturer: Hi-Healthcare, Inc
Category: otc | Type: HUMAN OTC DRUG LABEL
Date: 20200720

ACTIVE INGREDIENTS: FEXOFENADINE HYDROCHLORIDE 180 mg/1 1
INACTIVE INGREDIENTS: ANHYDROUS LACTOSE; SILICON DIOXIDE; STARCH, CORN; CROSCARMELLOSE SODIUM; HYPROMELLOSE, UNSPECIFIED; LACTOSE MONOHYDRATE; POLYETHYLENE GLYCOL, UNSPECIFIED; FERRIC OXIDE RED; STEARIC ACID; TITANIUM DIOXIDE; FERRIC OXIDE YELLOW

Hi-HealthCare Allergillic

Active ingredient (in each tablet)

Fexofenadine HCl 180 mg

Purpose

Antihistamine

Uses

Temporarily relieves these symptoms due to hay fever or other upper respiratory allergies:

▪ running nose ▪ itchy, watery eyes

▪ sneezing ▪ itching of the nose or throat

WARNINGS

Warnings: Do not use if you have ever had an allergic reaction to this product or any of its ingredients.

Ask a doctor before use if you have kidney disease. Your doctor should determine if you need a different dose.

When using this product

▪ Do not take more than directed

▪ Do not take at the same time as aluminium or magnesium antacids

▪ Do not take with fruit juices (See Directions)

▪ Stop use and ask a doctor if an allergic reaction to this product occurs. Seek medical help right away.

▪ If pregnant or breast-feeding, ask a health professional before use.

▪ Keep out of reach of children. In case of overdose, get medical help or contact a Poison Control Center right away.

DOSAGE AND ADMINISTRATION

Directions: ▪ Adults and children 12 years of age and over: take one 180 mg tablet with water once a day; do not take more than 1 table in 24 hours ▪ Children under 12 years of age: do not use ▪ Adults 65 years of age and older: ask a doctor ▪ Consumers with kidney disease: ask a doctor

Other information:

• Safety sealed: do not use if carton is opened or if printed foil inner seal on bottle is torn or missing • Store between 68° and 77 °F (20° and 25°C) • Protect from excessive moisture

Inactive ingredients:

anhydrous lactose, colloidal silicon dioxide, corn starch, croscarmellose sodium, hypromellose, lactose monohydrate, polyethylene glycol, pregelatinized starch (maize), red iron oxide, stearic acid, titanium dioxide and yellow iron oxide.

Questions?

Call toll-free 1-877-578-6288 / www.hi-healthcare.com

CLINICALLY PROVEN AND DOCTOR RECOMMENDED

Non-Drowsy

INDOOR / OUTDOOR ALLERGY RELIEF

• Sneezing

• Itchy, Watery eyes

• Runny Nose

• Itchy Nose or Throat

24 HOURS

Manufactured by:

A FDA Registered Facility

Distributed by:
HI-HEALTHCARE (USA), INC.
Fremont, CA 94539

proudly made in the u.s.a